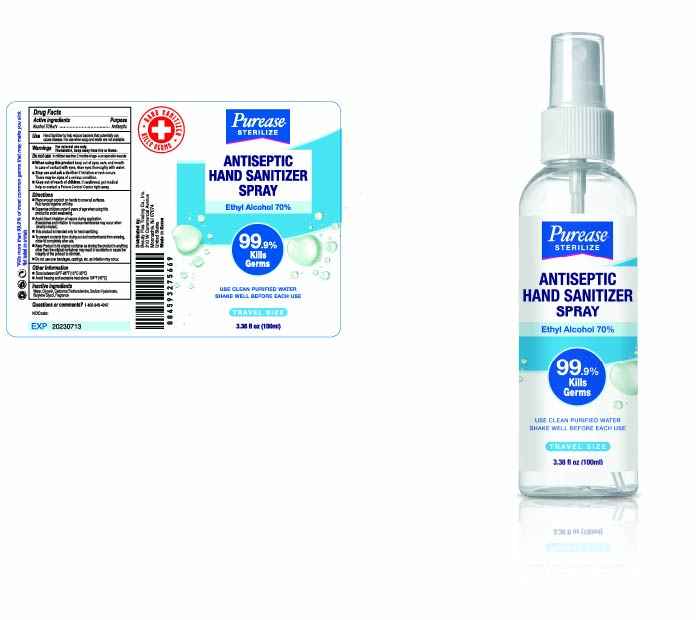 DRUG LABEL: PUREASE HAND SANITIZERspray
NDC: 78399-100 | Form: SPRAY
Manufacturer: Beauty Plus Trading Co., Inc.
Category: otc | Type: HUMAN OTC DRUG LABEL
Date: 20200715

ACTIVE INGREDIENTS: ALCOHOL 70 mL/100 mL
INACTIVE INGREDIENTS: GLYCERIN; CARBOMER HOMOPOLYMER, UNSPECIFIED TYPE; WATER; BUTYLENE GLYCOL; HYALURONATE SODIUM; TROLAMINE

PUREASE HAND SANITIZER SPRAY 100 mL : 78399-100-01